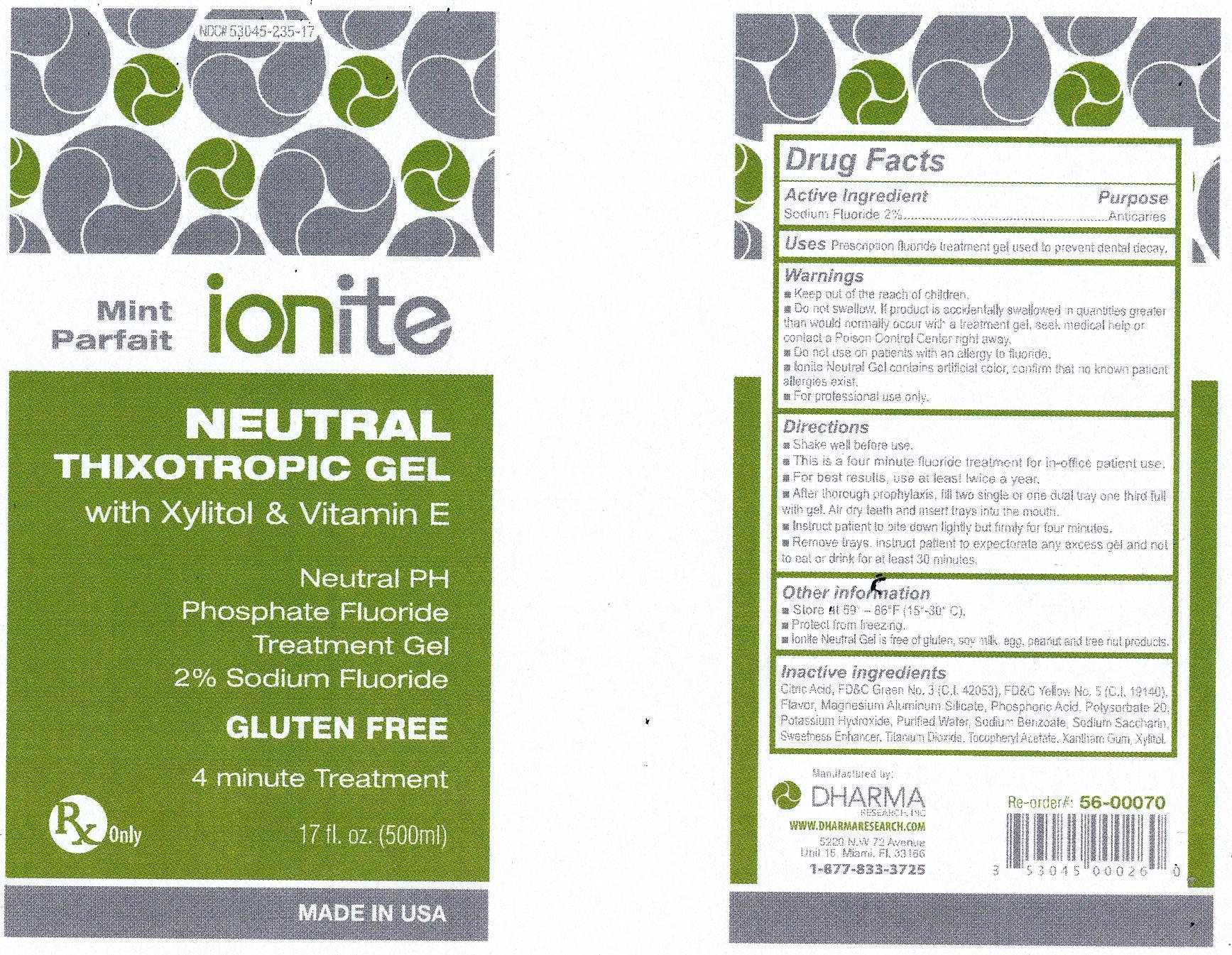 DRUG LABEL: Ionite APF
NDC: 53045-235 | Form: GEL
Manufacturer: Dharma Research, inc.
Category: prescription | Type: HUMAN PRESCRIPTION DRUG LABEL
Date: 20201118

ACTIVE INGREDIENTS: SODIUM FLUORIDE 4.41 g/490 g
INACTIVE INGREDIENTS: CITRIC ACID MONOHYDRATE; FD&C GREEN NO. 3; FD&C YELLOW NO. 5; MAGNESIUM ALUMINUM SILICATE; PHOSPHORIC ACID; POLYSORBATE 20; POTASSIUM HYDROXIDE; WATER; SODIUM BENZOATE; SACCHARIN SODIUM; TITANIUM DIOXIDE; .ALPHA.-TOCOPHEROL ACETATE, DL-; XANTHAN GUM; XYLITOL

STORAGE AND HANDLING

- Store at 59o - 86oF (15o - 30oC)
- Protect from freezing
- Ionite APF Gel is free of gluten, soymilk, egg peanut and free of nut products

INACTIVE INGREDIENT

Citric Acid, FD & C Green No. 3 (C.I. 42053), FD & C Yellow No. 5 (C.I. 19140), Flavor, Magnesium Aluminum Silicate, Phosphoric Acid, Polysorbate 20, Potassium Hydroxide, Purified Water, Sodium Benzoate, Sodium Saccharin, Sweetness Enhancer, Titanium Dioxide, Tocopheryl Acetate, Xantham Gum, Xylitol

WARNINGS AND PRECAUTIONS

- Keep out of the reach of children.
- Do not swallow. If product is accidentally swallowed in quantities greater than would normally occur with a treatment gel, seek medical help or contact a Poison Control Center right away.
- Do not use on patients with an allergy Fluoride.
- Ionite Neutral Gel contains artificial color, confirm that no known patient allergies exist.
- For professional use only.

- Shake well before use.
- This is a four minute or one minute Fluoride gel for in-office patient use.
- For best results, use at least twice a year.
- After thorough prophylaxis, fill two single or one dual tray one third full with gel. Air dry teeth and insert trays into the mouth.
- Instruct patient to bite down lightly but firmly for one minute (80% effectiveness) or four minutes (100% effectiveness)
- Remove trays, instruct patient to expectorate any excess gel and not to eat or drink for at least 30 minutes